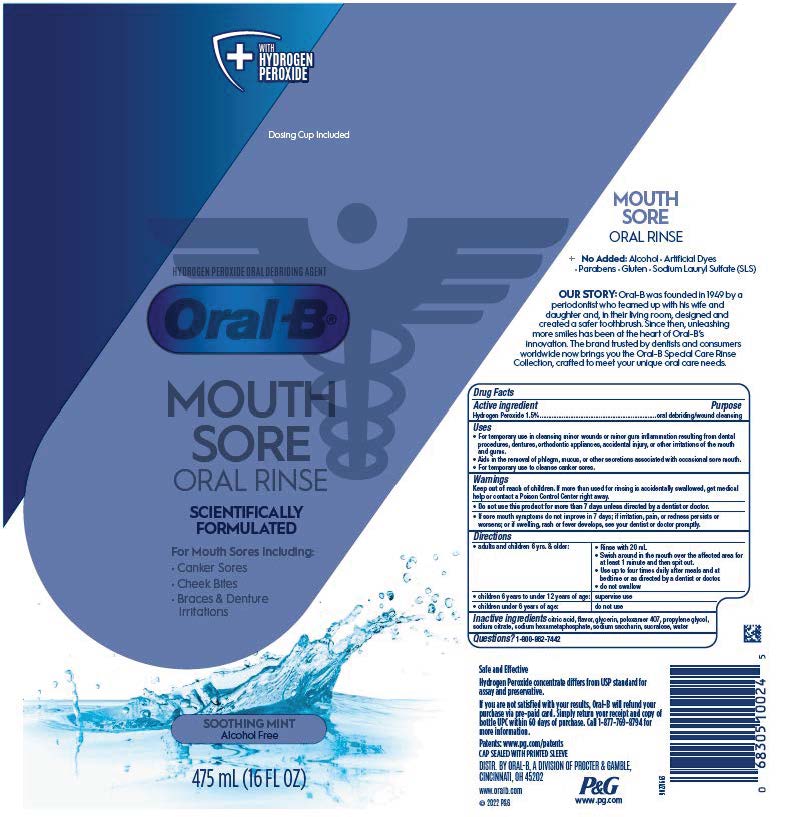 DRUG LABEL: Oral B Mouth Sore
NDC: 84126-603 | Form: RINSE
Manufacturer: The Procter & Gamble Manufacturing Company
Category: otc | Type: HUMAN OTC DRUG LABEL
Date: 20250731

ACTIVE INGREDIENTS: HYDROGEN PEROXIDE 0.03 mL/20 mL
INACTIVE INGREDIENTS: WATER; GLYCERIN; SODIUM CITRATE; SACCHARIN SODIUM; POLOXAMER 407; SUCRALOSE; SODIUM POLYMETAPHOSPHATE; PROPYLENE GLYCOL; CITRIC ACID MONOHYDRATE

Oral-B Mouth Sore Special Care Rinse

Drug Facts

Active ingredient

Hydrogen Peroxide 1.5%

Purpose

oral debriding/wound cleansing

Uses

- For temporary use in cleansing minor wounds or minor gum inflammation resulting from dental procedures, dentures, orthodontic appliances, accidental injury, or other irritations of the mouth and gums.
- Aids in the removal of phlegm, mucus, or other secretions associated with occasional sore mouth.
- For temporary use to cleanse canker sores.

Warnings

- Do not use this product for more than 7 days unless directed by a dentist or doctor.
- If sore mouth symptoms do not improve in 7 days; if irritation, pain, or redness persists or worsens; or if swelling, rash or fever develops, see your dentist or doctor promptly.

Keep out of reach of children.If more than used for rinsing is accidentally swallowed, get medical help or contact a Poison Control Center right away.

Directions

• adults and children 6 yrs. & older:

Rinse with 20 mL

Swish around in the mouth over the affected area for at least 1 minute and then spit out.

Use up to four times daily after meals and at bedtime or as directed by a dentist or doctor.

do not swallow

- children 6 years to under 12 years of age:

supervise use

- children under 6 years of age:

do not use

Inactive ingredients

citric acid, flavor, glycerin, poloxamer 407, propylene glycol, sodium citrate, sodium hexametaphosphate, sodium saccharin, sucralose, water

Questions?

1-800-862-7442

DISTR. BY ORAL-B, A DIVISION

OF PROCTER & GAMBLE,

CINCINNATI, OH 45202

PRINCIPAL DISPLAY PANEL - 475 mL Bottle Label

+ WITH HYDROGEN PEROXIDE

Dosing Cup Included

HYDROGEN PEROXIDE ORAL DEBRIDING AGENT

Oral-B

MOUTH SORE

ORAL RINSE

SCIENTIFICALLY

FORMULATED

For Mouth Sores Including:

- Canker Sores
- Cheek Bites
- Braces & Denture Irritations

SOOTHING MINT

475 mL (16 FL OZ)